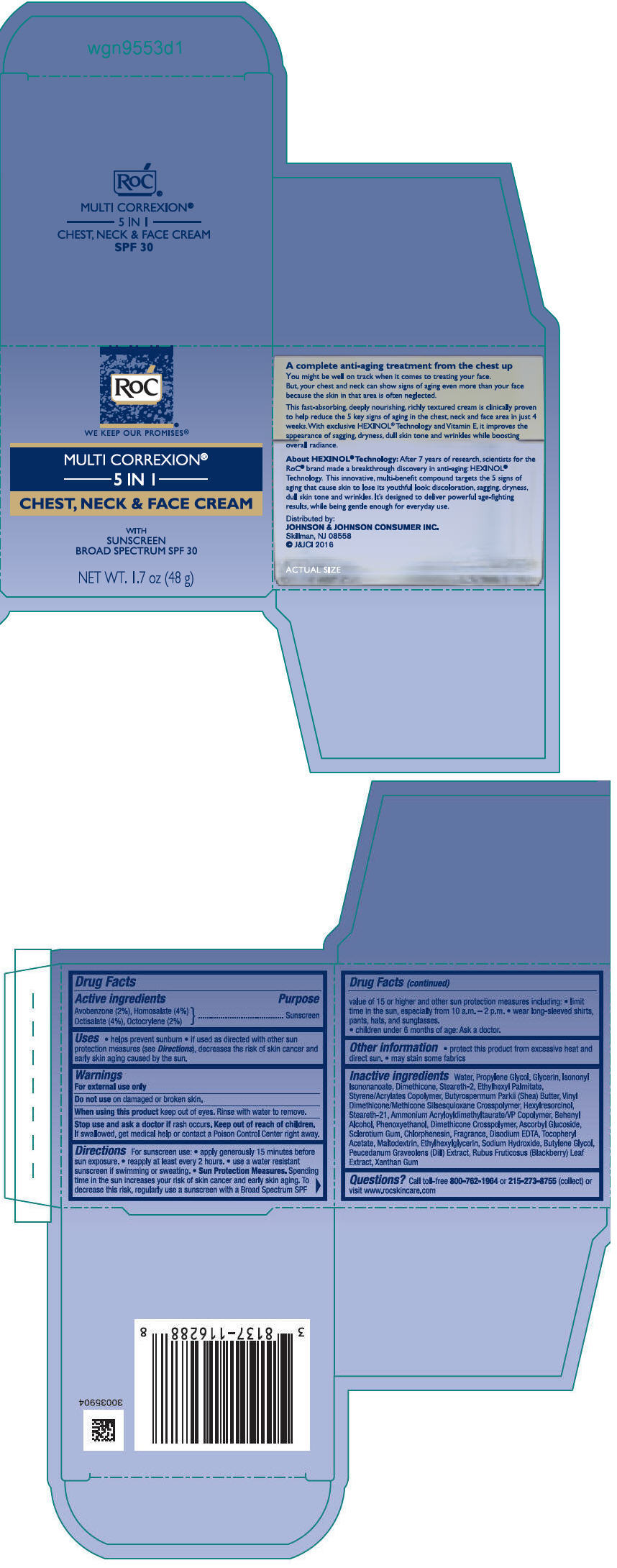 DRUG LABEL: ROC MULTI CORREXION 5 IN 1 CHEST, NECK AND FACE SUNSCREEN BROAD SPECTRUM SPF 30
NDC: 73496-003 | Form: LOTION
Manufacturer: ROC Skincare
Category: otc | Type: HUMAN OTC DRUG LABEL
Date: 20191204

ACTIVE INGREDIENTS: AVOBENZONE 20 mg/1 g; HOMOSALATE 40 mg/1 g; OCTISALATE 40 mg/1 g; OCTOCRYLENE 20 mg/1 g
INACTIVE INGREDIENTS: WATER; PROPYLENE GLYCOL; GLYCERIN; ISONONYL ISONONANOATE; DIMETHICONE; STEARETH-2; ETHYLHEXYL PALMITATE; STYRENE/ACRYLAMIDE COPOLYMER (500000 MW); SHEA BUTTER; VINYL DIMETHICONE/METHICONE SILSESQUIOXANE CROSSPOLYMER; HEXYLRESORCINOL; STEARETH-21; AMMONIUM ACRYLOYLDIMETHYLTAURATE/VP COPOLYMER; DOCOSANOL; PHENOXYETHANOL; DIMETHICONE CROSSPOLYMER (450000 MPA.S AT 12% IN CYCLOPENTASILOXANE); ASCORBYL GLUCOSIDE; BETASIZOFIRAN; CHLORPHENESIN; EDETATE DISODIUM ANHYDROUS; MALTODEXTRIN; ETHYLHEXYLGLYCERIN; SODIUM HYDROXIDE; BUTYLENE GLYCOL; DILL; RUBUS FRUTICOSUS LEAF; XANTHAN GUM; .ALPHA.-TOCOPHEROL ACETATE, DL-

ROC MULTI CORREXION 5 IN 1 CHEST, NECK AND FACE SUNSCREEN BROAD SPECTRUM SPF 30.jpg

PACKAGE LABEL.PRINCIPAL DISPLAY PANEL

OTC - PURPOSE

Active ingredientsPurpose

Avobenzone 2% Sunscreen Homosalate 4% Sunscreen Octisalate 4% Sunscreen Octocrylene 2% Sunscreen

OTC - KEEP OUT OF REACH OF CHILDREN

Keep out of reach of children. If swallowed, get medical help or contact a Poison Control Center right away

USES

Helps prevent sunburnif used as directed with other sun protection measures (see Directions), decreases the risk of skin cancer and early skin aging caused by the sun

WARNINGS

For external use only

Do not use on damaged or broken skin

When using this product keep out of eyes. Rinse with water to remove.

Stop use and ask a doctor if rash occurs

DIRECTIONS

For sunscreen use:apply generously and evenly15 minutes before sun exposurereapply at least every 2 hoursuse a water resistant sunscreen if swimming or sweatingSun Protection Measures. Spending time in the sun increases your risk of skin cancer and early skin aging. To decrease this risk, regularly use a sunscreen with a Broad Spectrum SPF value of 15 or higher and other sun protection measures including:limit time in the sun, especially from 10 a.m. – 2 p.m.wear long-sleeved shirts, pants, hats, and sunglasseschildren under 6 months of age: Ask a doctor

INACTIVE INGREDIENTS

Water, Propylene Glycol, Glycerin, Isononyl Isononanoate, Dimethicone, Steareth-2, Ethylhexyl Palmitate, Styrene/Acrylates Copolymer, Butyrospermum Parkii (Shea) Butter, Vinyl Dimethicone/Methicone Silsesquioxane Crosspolymer, Hexylresorcinol, Steareth-21, Ammonium Acryloyldimethyltaurate/VP Copolymer, Behenyl Alcohol, Phenoxyethanol, Dimethicone Crosspolymer, Ascorbyl Glucoside, Sclerotium Gum, Chlorphenesin, Fragrance, Disodium EDTA, Tocopheryl Acetate, Maltodextrin, Ethylhexylglycerin, Sodium Hydroxide, Butylene Glycol, Peucedanum Graveolens (Dill) Extract, Rubus Fruticosus (Blackberry) Leaf Extract, Xanthan Gum

QUESTIONS?

Call 1-800-RoC-1964 (1-800-762-1964); Outside US, dial collect 215-273-8755, or visit ww.rocskincare.com